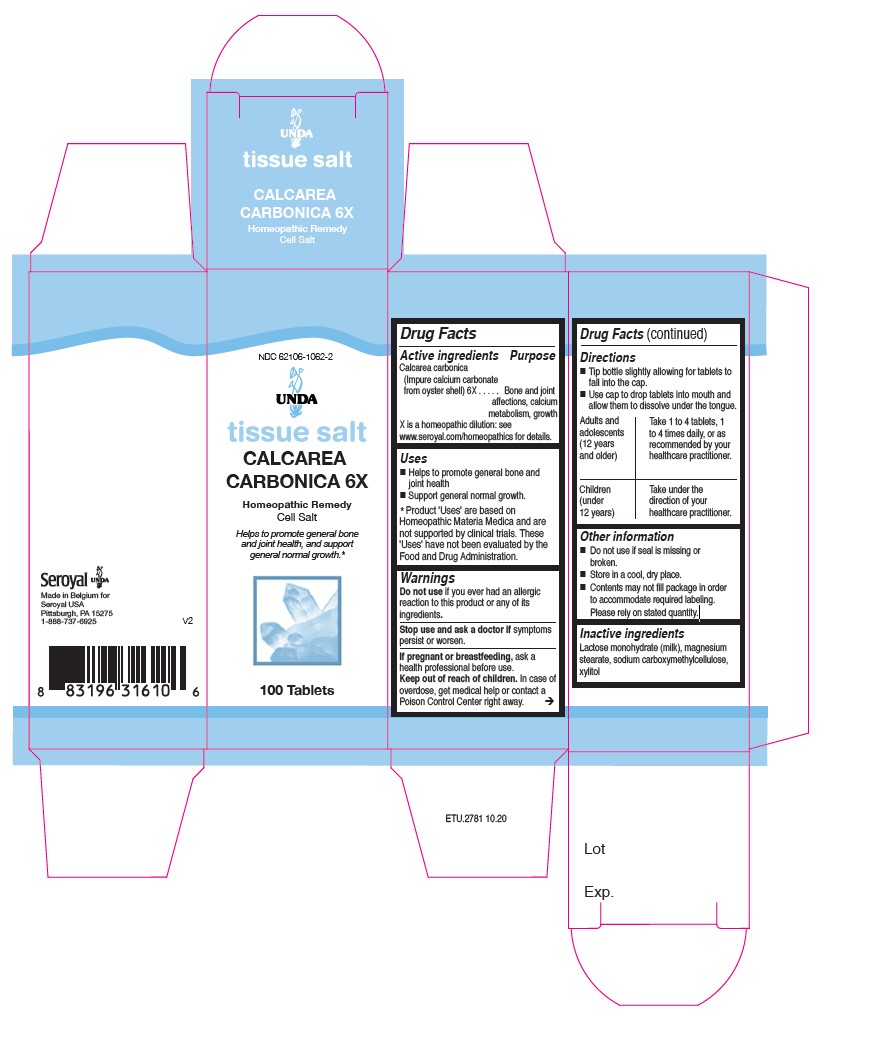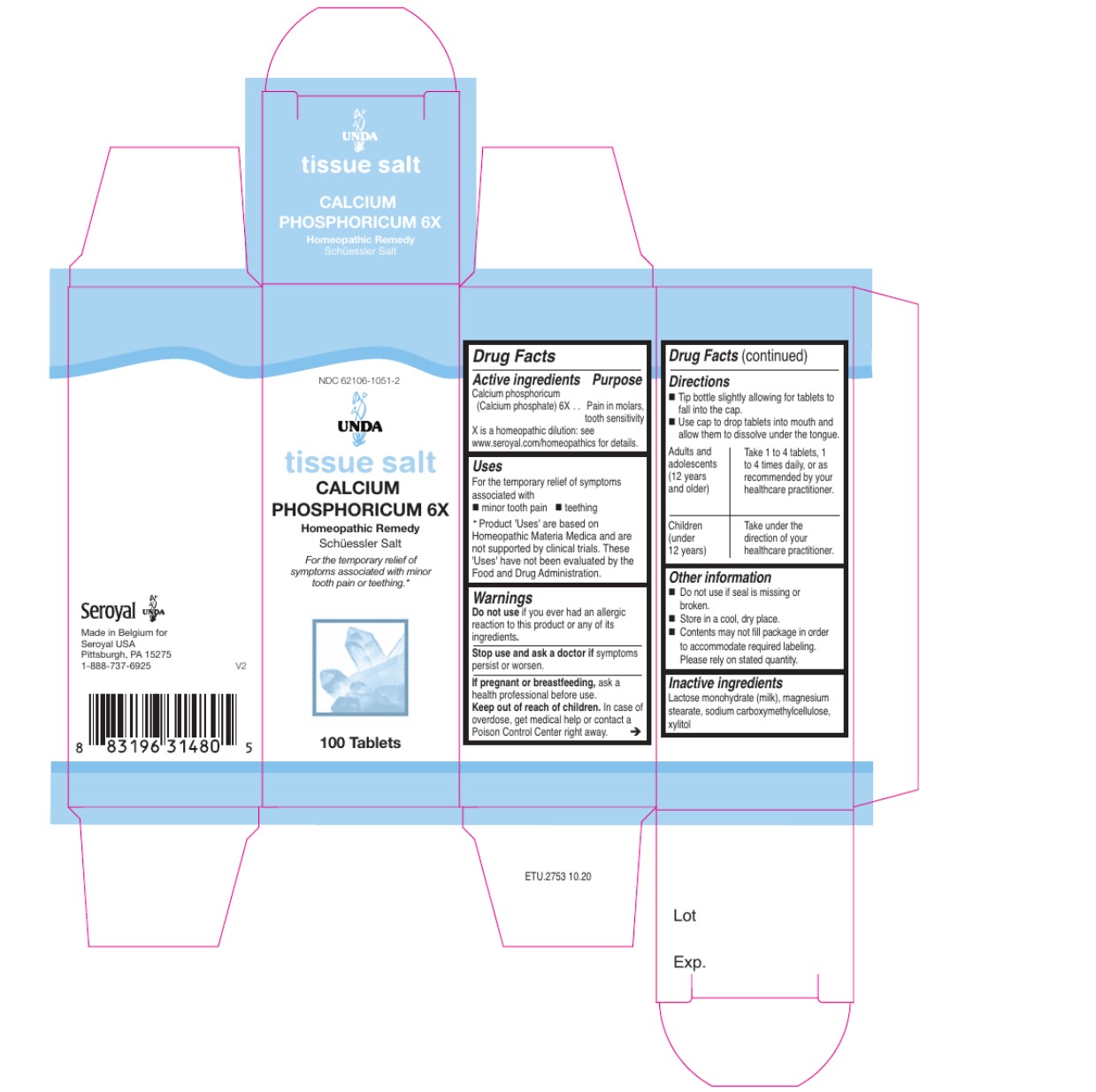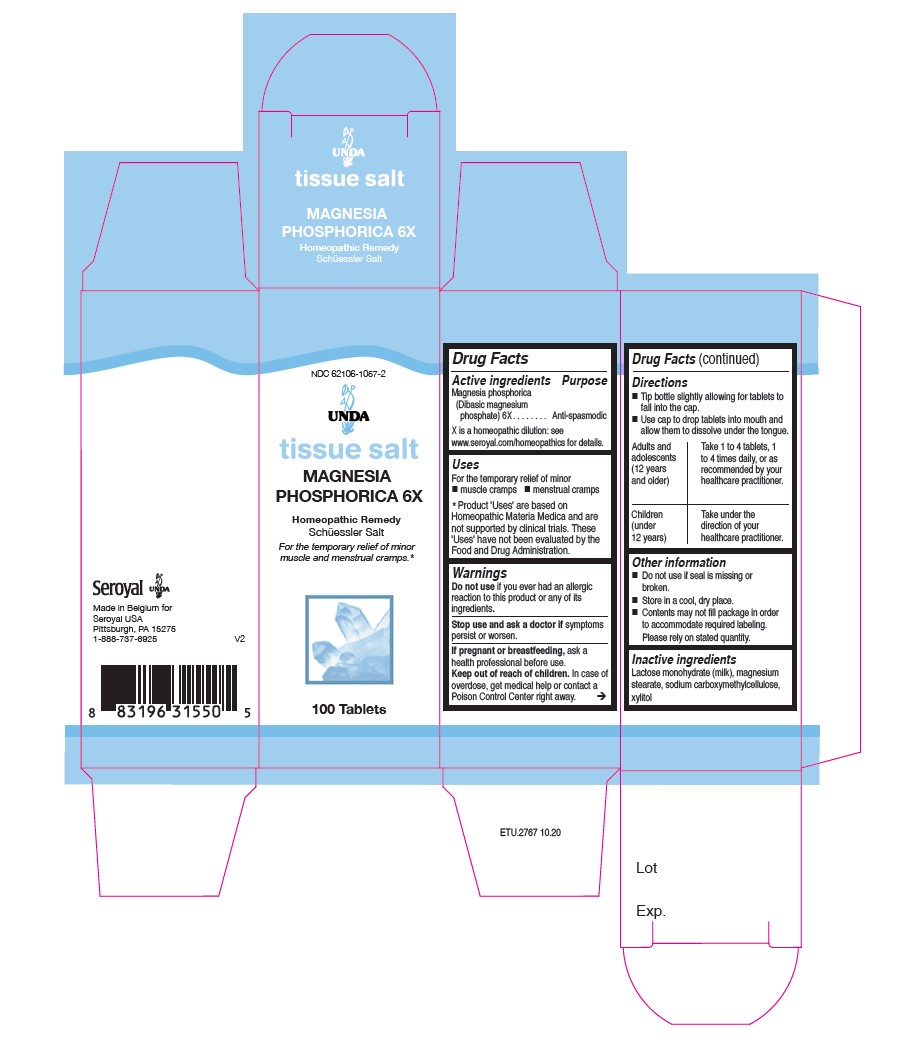 DRUG LABEL: MAGNESIA PHOSPHORICA 6x
NDC: 62106-1057 | Form: TABLET
Manufacturer: Seroyal USA
Category: homeopathic | Type: HUMAN OTC DRUG LABEL
Date: 20210716

ACTIVE INGREDIENTS: MAGNESIUM PHOSPHATE, DIBASIC TRIHYDRATE 6 [hp_X]/1 1
INACTIVE INGREDIENTS: LACTOSE MONOHYDRATE; MAGNESIUM STEARATE; CARBOXYMETHYLCELLULOSE SODIUM; XYLITOL

Unda Tissue Salts

Active Ingredients

Magnesia phosphorica (Dibasic magnesium phosphate) 6X

Uses

For the temporary relief of minor

muscle cramps

menstrual cramps

Warnings
Do not use if you ever had an allergic reaction to this product or any of its ingredients.
Stop use and ask a doctor if symptoms persist or worsen.
If pregnant or breastfeeding, ask a health professional before use.
Keep out of reach of children.

In case of overdose, get medical help or contact a Poison Control Center right away.

Stop use and ask a doctor if symptoms persist or worsen.

PREGNANCY OR BREAST FEEDING

If pregnant or breastfeeding, ask a healthcare professional before use.

Keep out of reach of children.

OVERDOSAGE

In case of overdose, get medical help or contact a Poison Control Center right away.

Inactive Ingredients:

Lactose monohydrate (milk),

magnesium stearate,

sodium carboxymethylcellulose,

xylitol

Directions

Tip bottle slightly allowing for tablets to fall into the cap.

Use cap to drop tablets into mouth and allow them to dissolve under the tongue.
Adults and Adolescents (12 years and older): Take 1 to 4 tablets, one to
four times daily, or as recommended by your healthcare practitioner.

Children (under 12 years): Take under the direction of your healthcare practitioner.

Uses
For the temporary relief of minor
muscle cramps

menstrual cramps

Directions

Tip bottle slightly allowing for tablets to fall into the cap.
Use cap to drop tablets into mouth and allow them to dissolve under the tongue.
Adults and Adolescents (12 years and older): Take 1 to 4 tablets, one to
four times daily, or as recommended by your healthcare practitioner.

Children (under 12 years): Take under the direction of your healthcare practitioner.

Active ingredients

Calcarea Carbonica (Impure Calcium Carbonate from oyster shell) 6X

Uses

Helps to promote general bone and joint health.

Support general normal growth.

Warnings
Do not use if you ever had an allergic
reaction to this product or any of its
ingredients.
Stop use and ask a doctor if symptoms
persist or worsen.
If pregnant or breastfeeding, ask a
health professional before use.
Keep out of reach of children. In case of
overdose, get medical help or contact a
Poison Control Center right away.

PREGNANCY OR BREAST FEEDING

If you are pregnant or breastfeeding, ask a healthcare practitioner before use.

Keep out of reach of children.

OVERDOSAGE

In case of overdose, get medical help or contact
a Poison Control Center right away.

Stop use and ask a doctor if symptoms
persist or worsen.

Inactive ingredients
Lactose monohydrate (milk), magnesium
stearate, sodium carboxymethylcellulose,
xylitol

Directions

Tip bottle slightly allowing for tablets to fall into the cap.
Use cap to drop tablets into mouth and allow them to dissolve under the tongue.
Adults and adolescents (12 years and older)

Take 1 to 4 tablets, one to four times daily, or as recommended by your healthcare practitioner.
Children (under 12 years)
Take under the direction of your healthcare practitioner.

Uses
Helps to promote general bone and joint health.
Support general normal growth.

Directions

Tip bottle slightly allowing for tablets to fall into the cap.
Use cap to drop tablets into mouth and allow them to dissolve under the tongue.
Adults and adolescents (12 years and older)

Take 1 to 4 tablets, one to four times daily, or as recommended by your healthcare practitioner.
Children (under 12 years)
Take under the direction of your healthcare practitioner.

Active ingredients

Calcium phosphoricum (calcium phosphate) 6X

Uses

For the temporary relief of symptoms associated with

minor tooth pain

teething

Warnings
Do not use if you ever had an allergic reaction to this product or any of its ingredients.
Stop use and ask a doctor if symptoms persist or worsen.
If pregnant or breastfeeding, ask a health professional before use.
Keep out of reach of children.

In case of overdose, get medical help or contact a Poison Control Center right away.

PREGNANCY OR BREAST FEEDING

If pregnant or breastfeeding, ask a healthcare professional before use.

Keep out of reach of children.

OVERDOSAGE

In case of overdose, get medical help or contact
a Poison Control Center right away.

Stop use and ask a doctor if symptoms persist or worsen.

Inactive Ingredients:

Lactose monohydrate (milk),

magnesum stearate,

sodium carboxymethlycellulose,

xylitol

Directions

Tip bottle slightly allowing for tablets to fall into the cap.
Use cap to drop tablets into mouth and allow them to dissolve under the tongue.
Adults and adolescents (12 years and older): Take 1 to 4 tablets, one to
four times daily, or as recommended by your healthcare practitioner.

Children (under 12 years): Take under the direction of your healthcare practitioner.

Indications

For the temporary relief of symptoms associated with

minor tooth pain

teething

Directions

Tip bottle slightly allowing for tablets to fall into the cap.
Use cap to drop tablets into mouth and allow them to dissolve under the tongue.
Adults and adolescents (12 years and older): Take 1 to 4 tablets, one to
four times daily, or as recommended by your healthcare practitioner.

Children (under 12 years): Take under the direction of your healthcare practitioner.

Other information
Do not use if seal is missing or broken.
Store in a cool, dry place.

Contents may not fill package in order
to accommodate required labeling.
Please rely on stated quantity.

Other information
Do not use if seal is missing or broken.
Store in a cool, dry place.

Contents may not fill package in order
to accommodate required labeling.
Please rely on stated quantity.

Other information
Do not use if seal is missing or
broken.
Store in a cool, dry place.
Contents may not fill package in order
to accommodate required labeling.
Please rely on stated quantity.

PACKAGE LABEL

NDC 62106-1062-2

UNDA

tissue salt

CALCAREA CARBONICA 6X

Homeopathic Remedy

Cell Salt

Helps to promote general bone and joint
health, and support general normal growth.

100 Tablets

PACKAGE LABEL

NDC 62106-1057-2

UNDA

tissue salt

MAGNESIA PHOSPHORICA 6X

Homeopathic Remedy

Schüessler Salt

For the temporary relief of minor
muscle and menstrual cramps.

100 Tablets

PACKAGE LABEL

NDC 62106-1051-2

UNDA

tissue salt

CALCIUM PHOSPHORICUM 6X

Homeopathic Remedy

Schüessler Salt

For the temporary relief of symptoms associated with minor tooth pain or teething.

100 Tablets